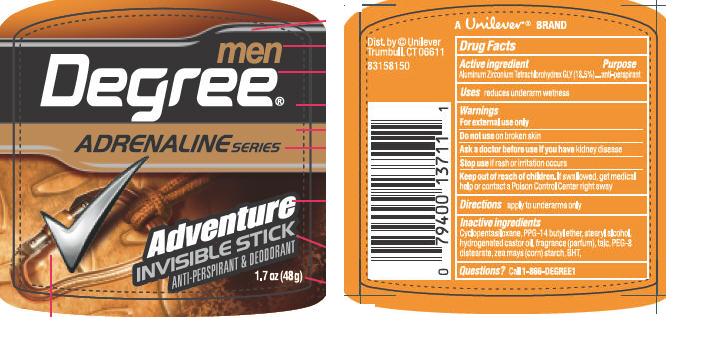 DRUG LABEL: Degree Men
NDC: 64942-1125 | Form: STICK
Manufacturer: Conopco Inc. d/b/a Unilever
Category: otc | Type: HUMAN OTC DRUG LABEL
Date: 20100909

ACTIVE INGREDIENTS: Aluminum Zirconium Tetrachlorohydrex GLY 18.5 g/100 g
INACTIVE INGREDIENTS: CYCLOMETHICONE 5; PPG-14 Butyl Ether; Stearyl Alcohol; HYDROGENATED CASTOR OIL; TALC; POLYETHYLENE GLYCOL 400; STARCH, CORN; BUTYLATED HYDROXYTOLUENE

Degree Men Adventure IS AP and Deod., PDP and drug facts

Active Ingredient

Aluminum Zirconium Tetrachlorohydrex GLY (18.5%)

PURPOSE

Enter section text here

INDICATIONS AND USAGE

Uses reduces underarm wetness

Warnings
For External Use Only

Do not use on broken skin

Ask a doctor before use if you have kidney disease

Stop use if rash or irritation occurs

Keep out of reach of children. If swallowed, get medical help or contact a Poison Control Center right away

DOSAGE AND ADMINISTRATION

Directions apply to underarms only

INACTIVE INGREDIENT

Cyclopentasiloxane
PPG-14 Butyl Ether
Stearyl Alcohol
Hydrogenated Castor Oil
Fragrance (Parfum)
Talc
PEG-8 Distearate
Zea Mays (Corn) Starch
BHT

Questions? Call 1-866-DEGREE1

PACKAGE LABEL

1.7 oz PDP